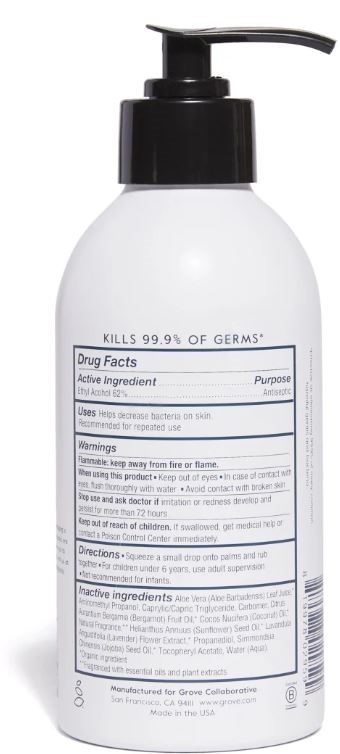 DRUG LABEL: HandSanitizerGelBloodOrange
NDC: 72496-1130 | Form: GEL
Manufacturer: Naturich Labs, Inc
Category: otc | Type: HUMAN OTC DRUG LABEL
Date: 20251230

ACTIVE INGREDIENTS: ALCOHOL 62 mL/100 mL
INACTIVE INGREDIENTS: WATER 32 mL/100 mL

Active Ingredient

Ethyl Alcohol 62%

Purpose

Antiseptic

Uses:

Helps decrease bacteria on skin. Recommended for repeated use

Warnings

Flammable: keep away from fire or flame.

When using this product

- Keep out of eyes

- In case of contact with eyes, flush thoroughly with water.

- Avoid contact with broken skin

Stop Use

Stop use and ask a doctor if irritation or redness develop and persist for more than 72 hours.

Keep out of reach of children.

If swallowed, get medical help or contact a Poison Control Center Immediately.

Directions:

Squeeze a small drop onto palms and rub together. For children under 6 years, use adult supervision. Not recommended for infants.

Inactive Ingredients:

Water (Aqua), Propanediol, Aloe Barbadensis (Aloe Vera) Leaf Juice, Caprylic/Capric Triglyceride, Cocos Nucifera (Coconut) Oil, Simmondsia Chinensis (Jojoba) Seed Oil, Helianthus Annuus (Sunflower) Seed Oil, Lavandula Angustifolia (Lavender) Flower Extract, Natural Fragrance*, Aminomethyl Propanol, Carbomer, Citrus Aurantium Bergamia (Bergamo!) Fruit Oil, Tocopheryl Acetate, Citral, Limonene, Linalool.

Other Information:

Store between 16-30C (59-86F).

Avoid freezing and excessive heat above 40C (104F)